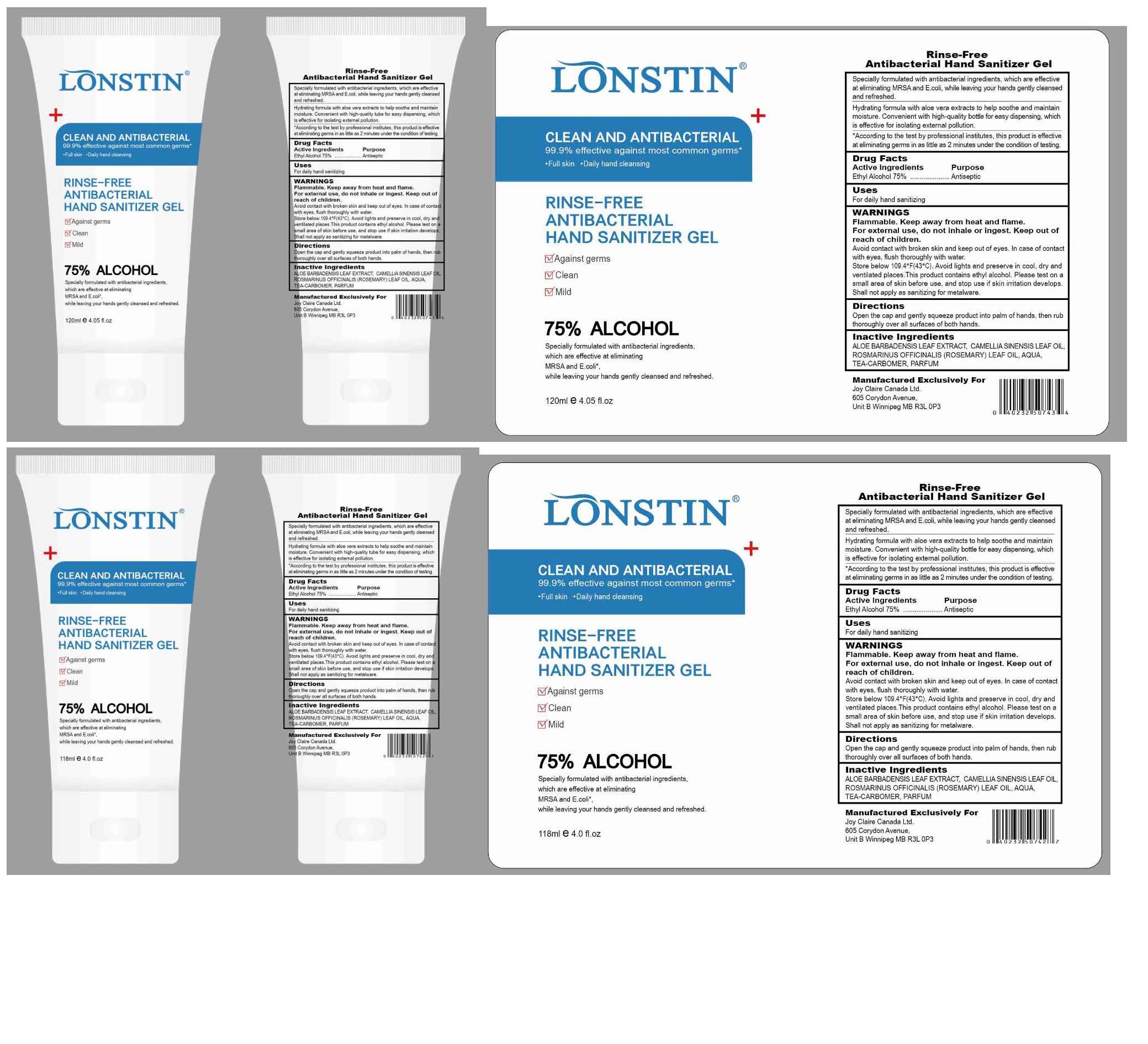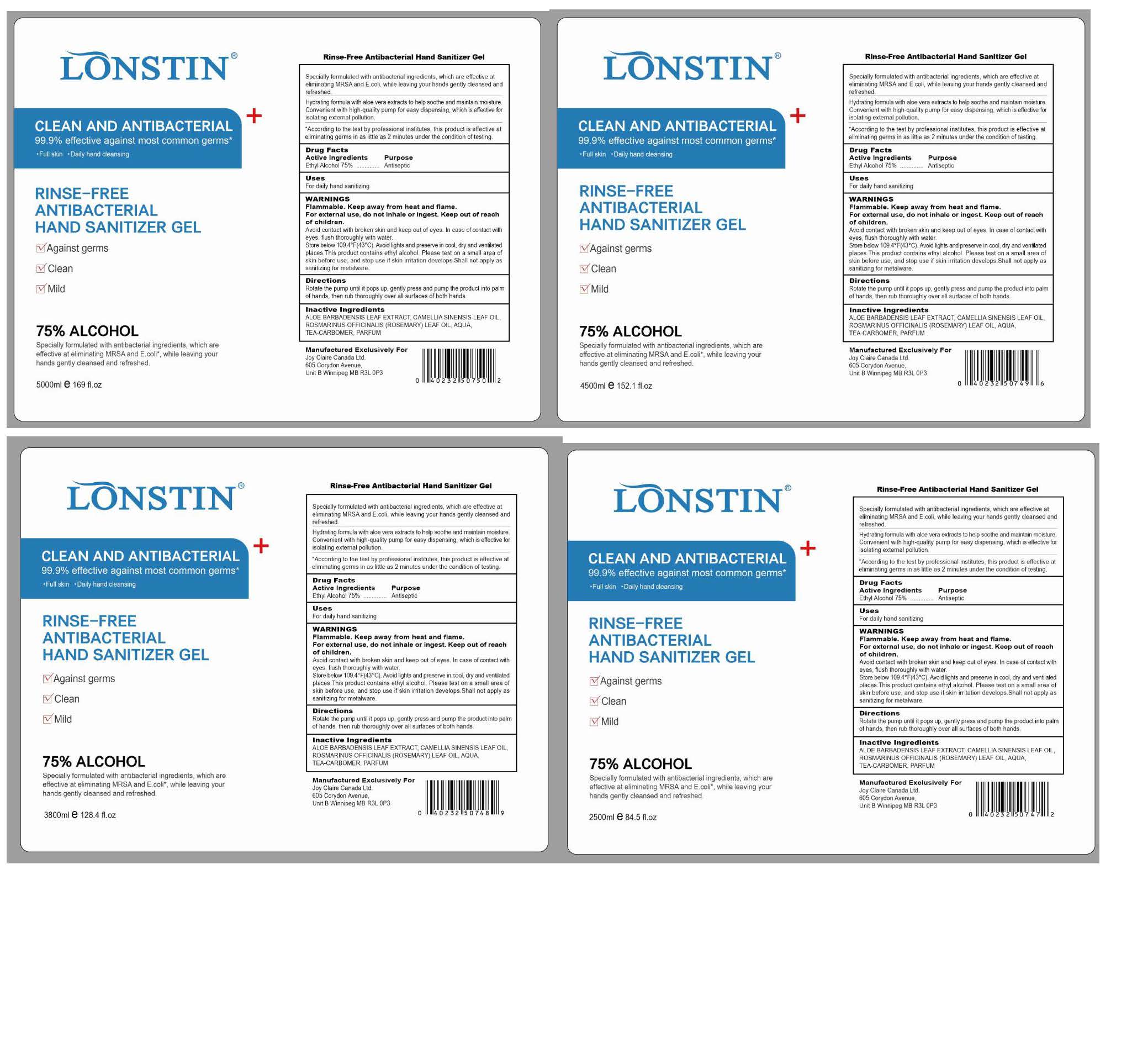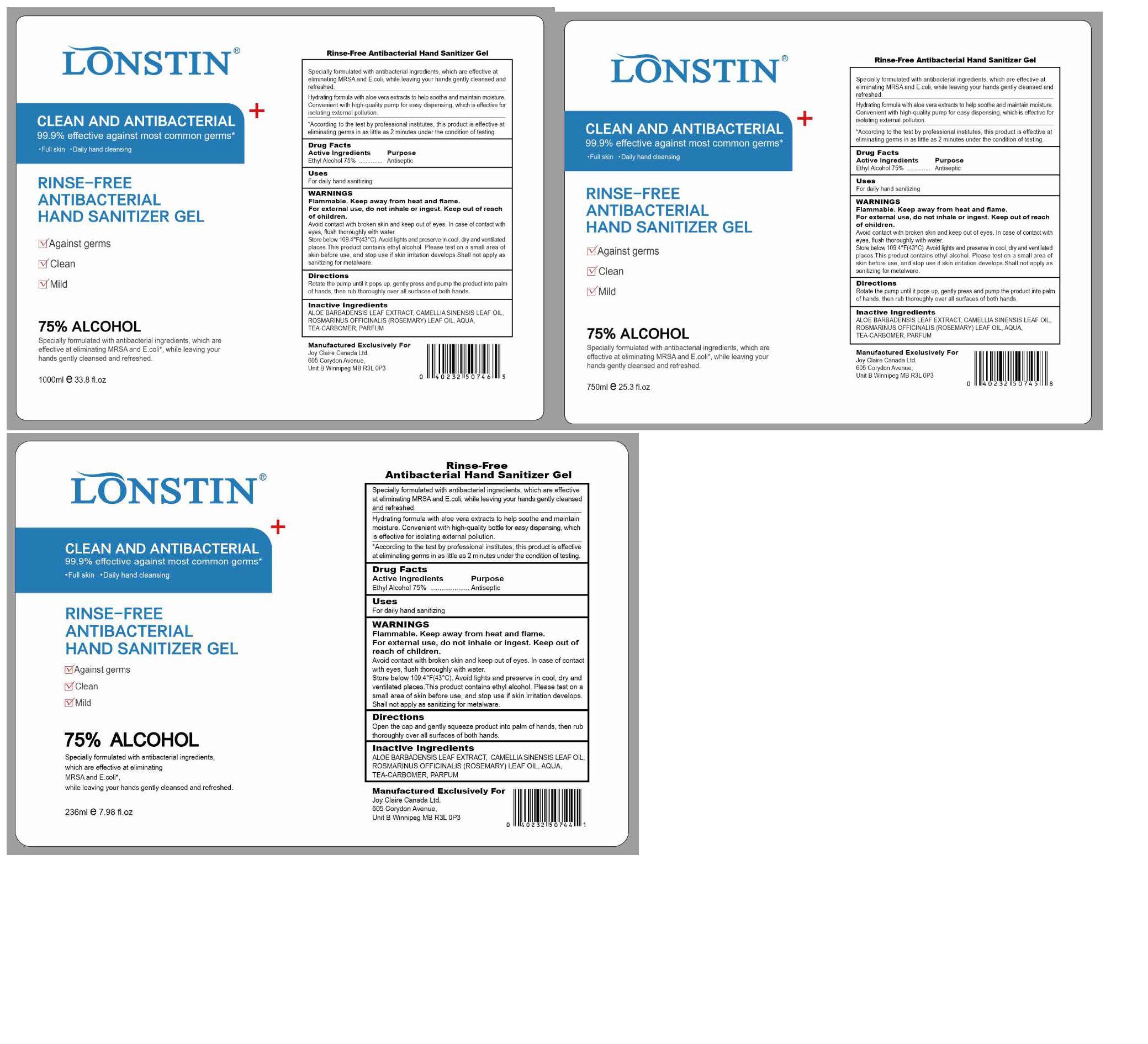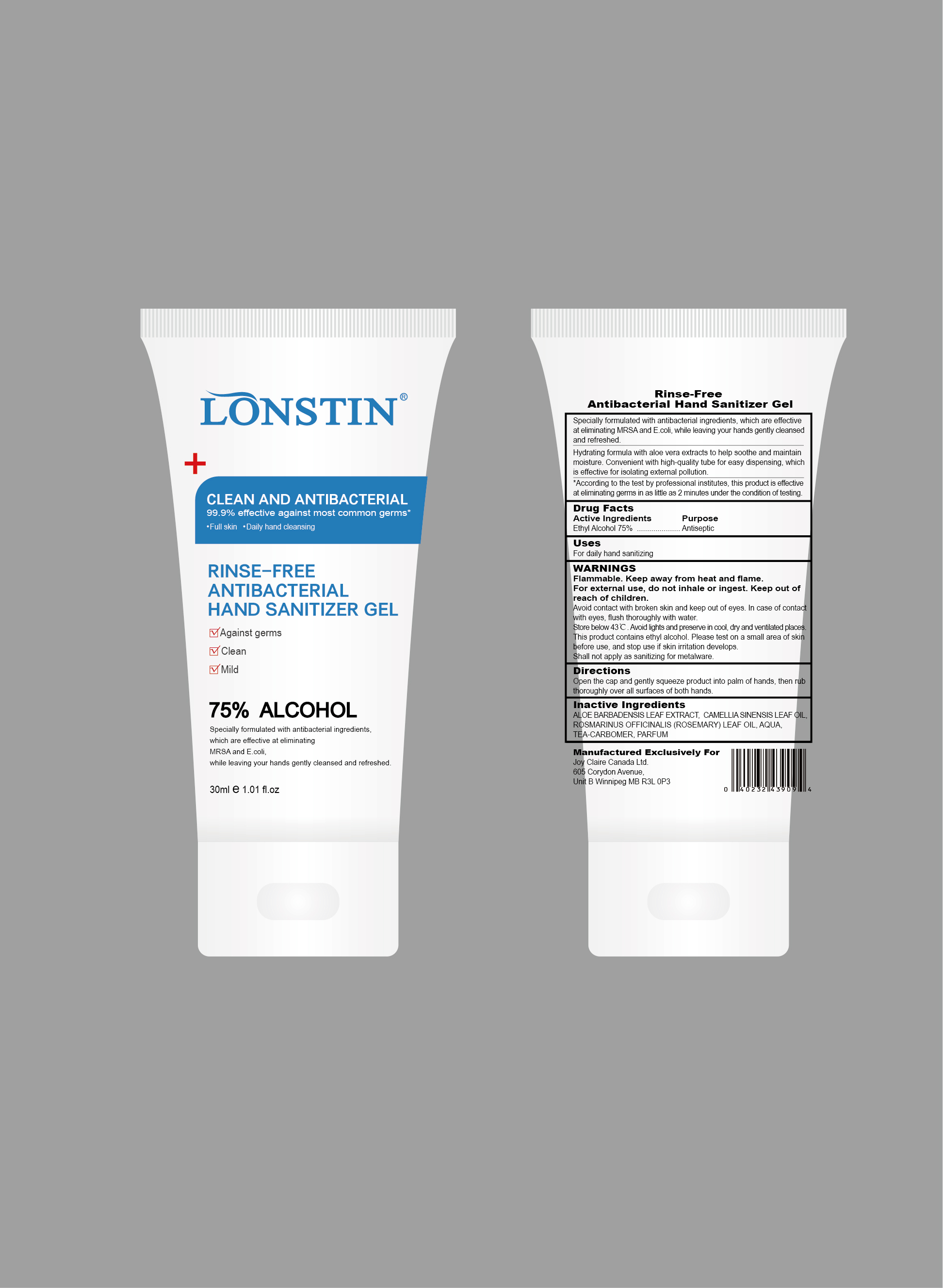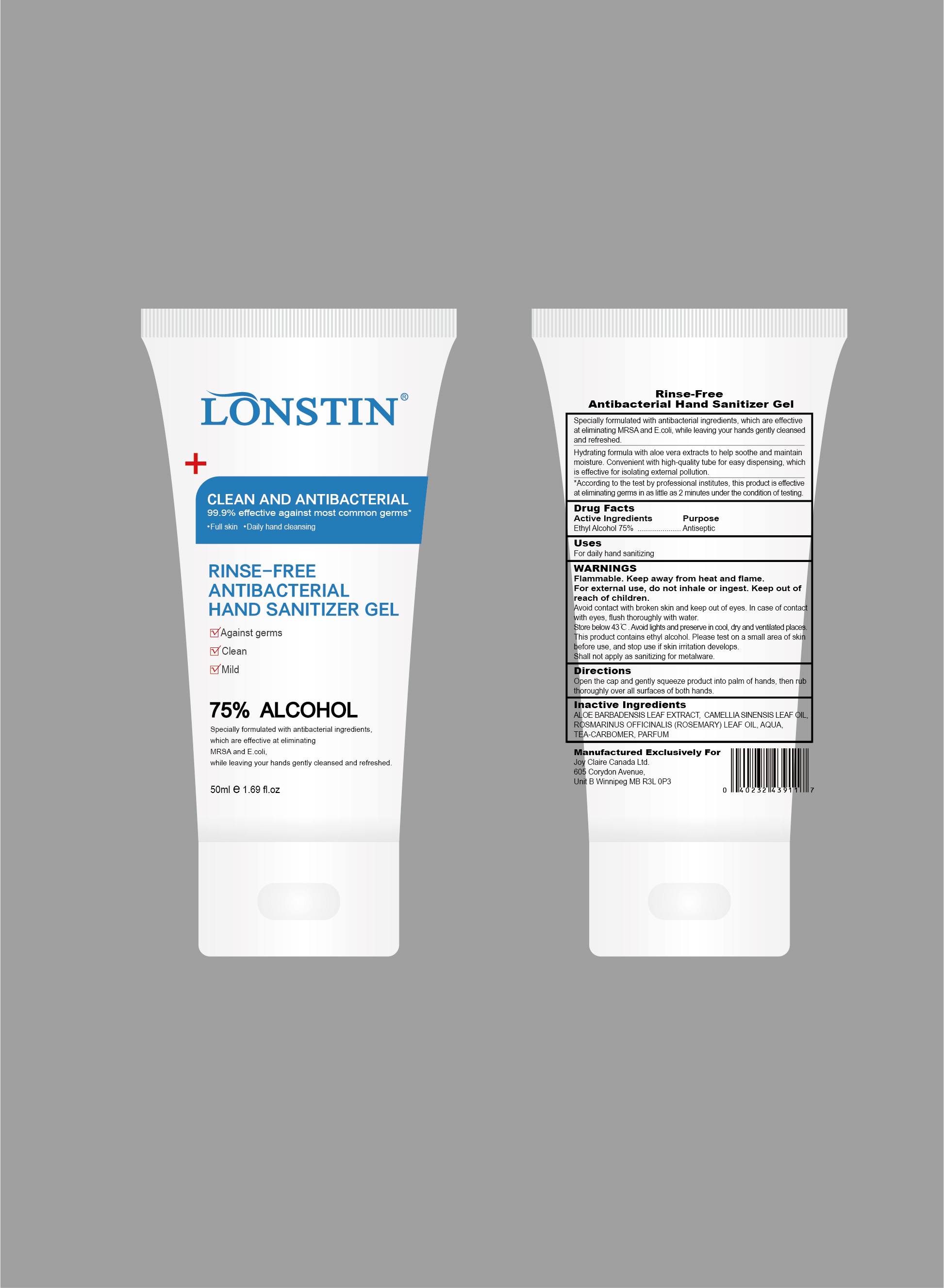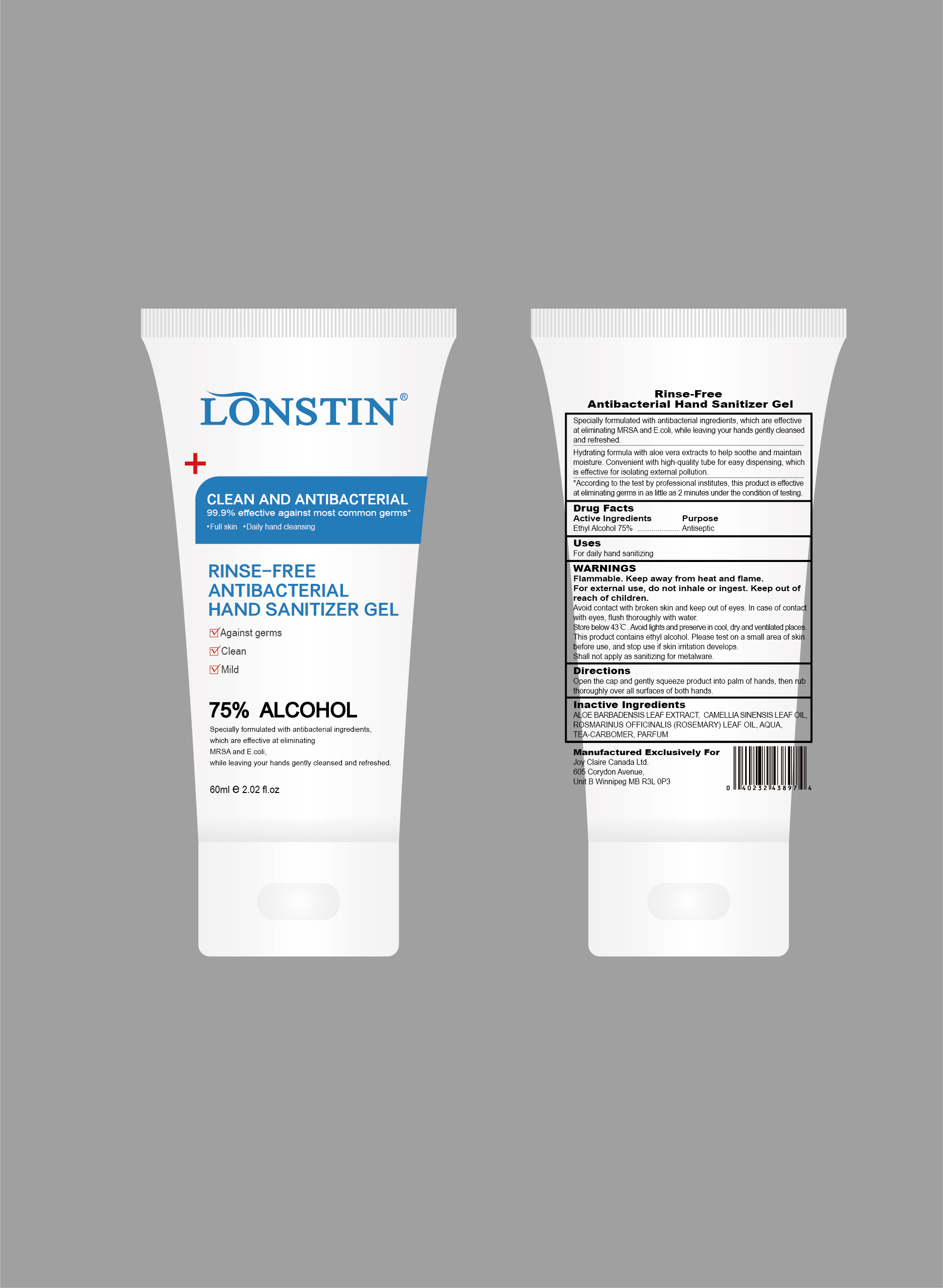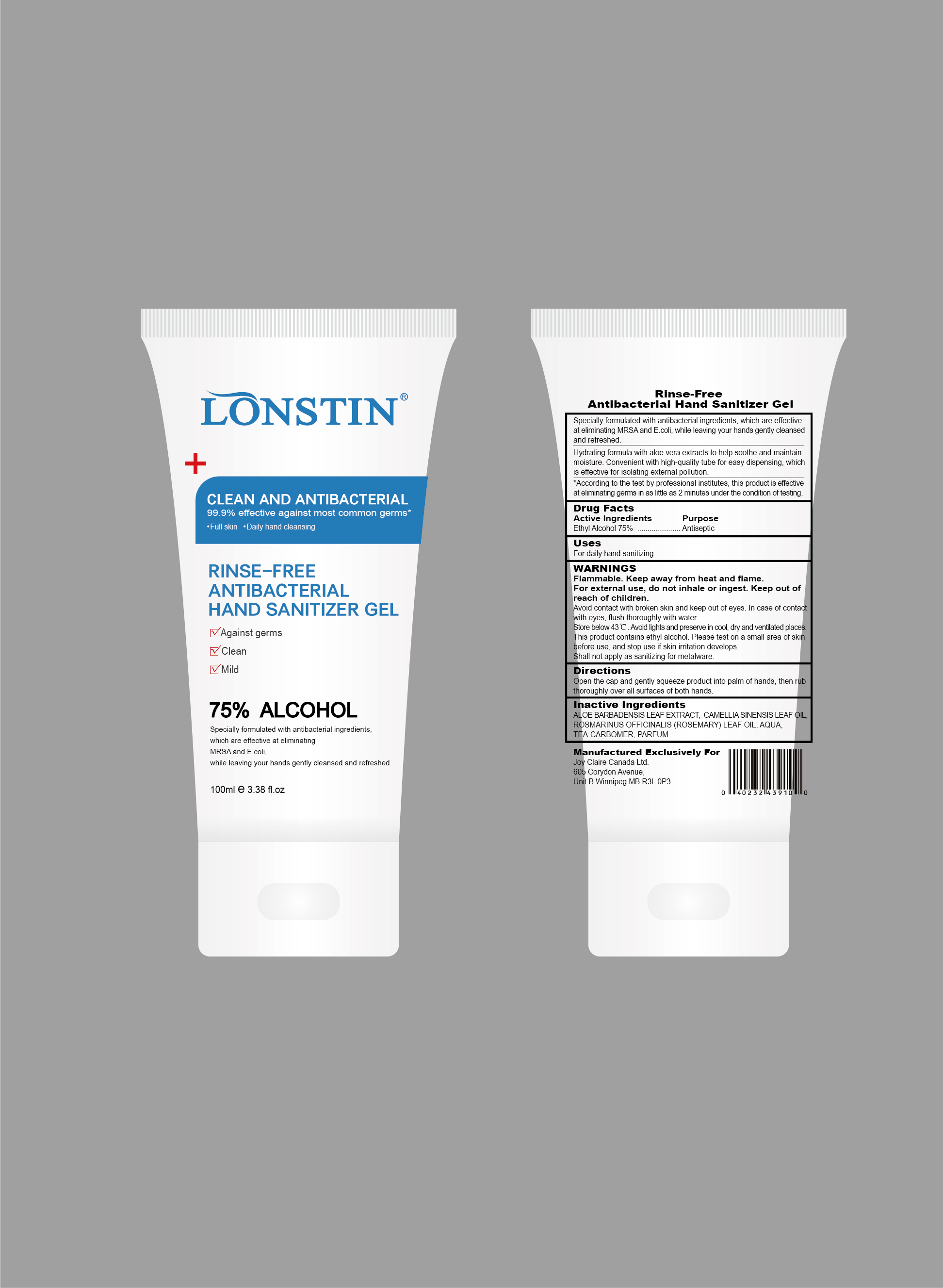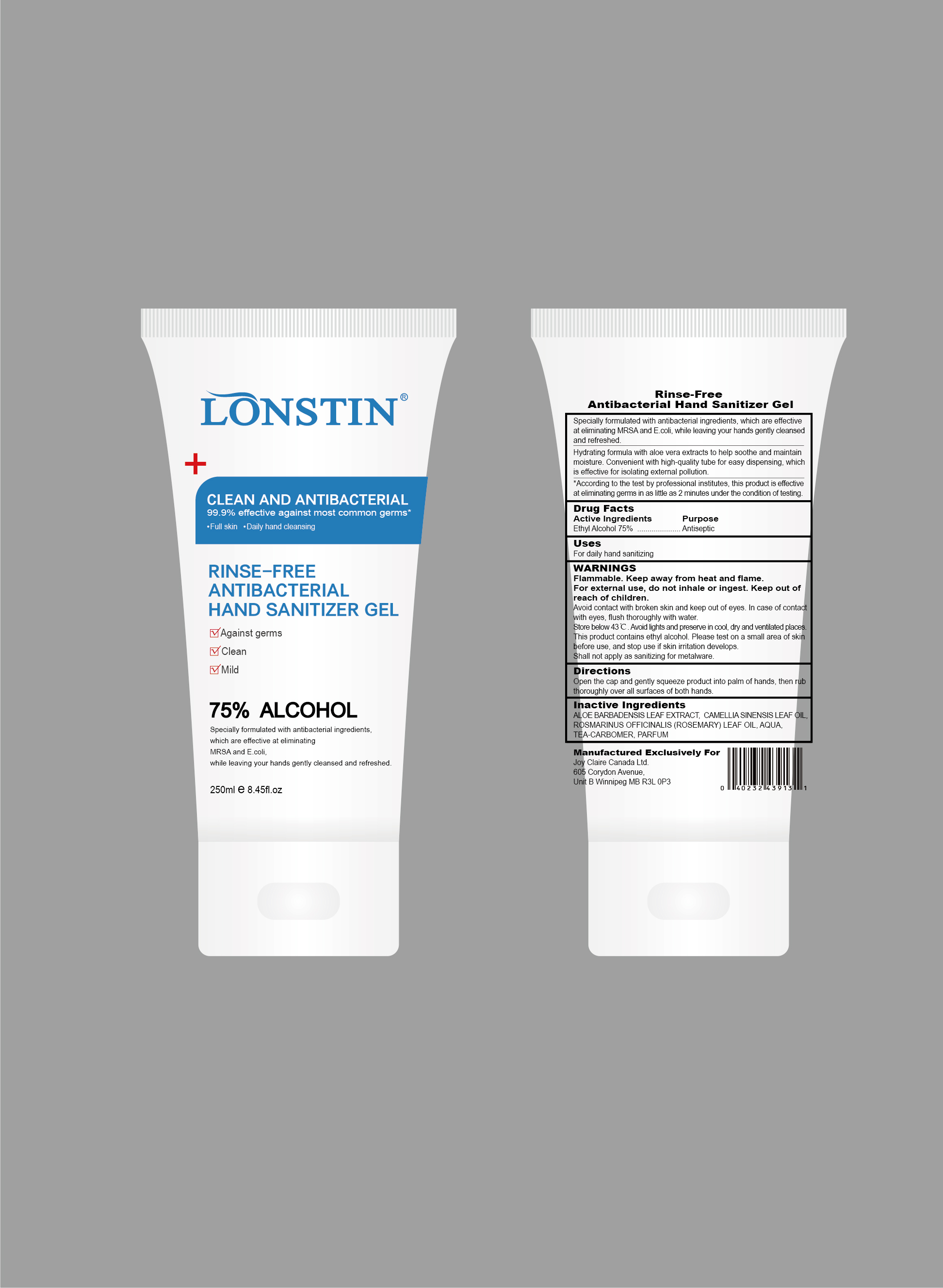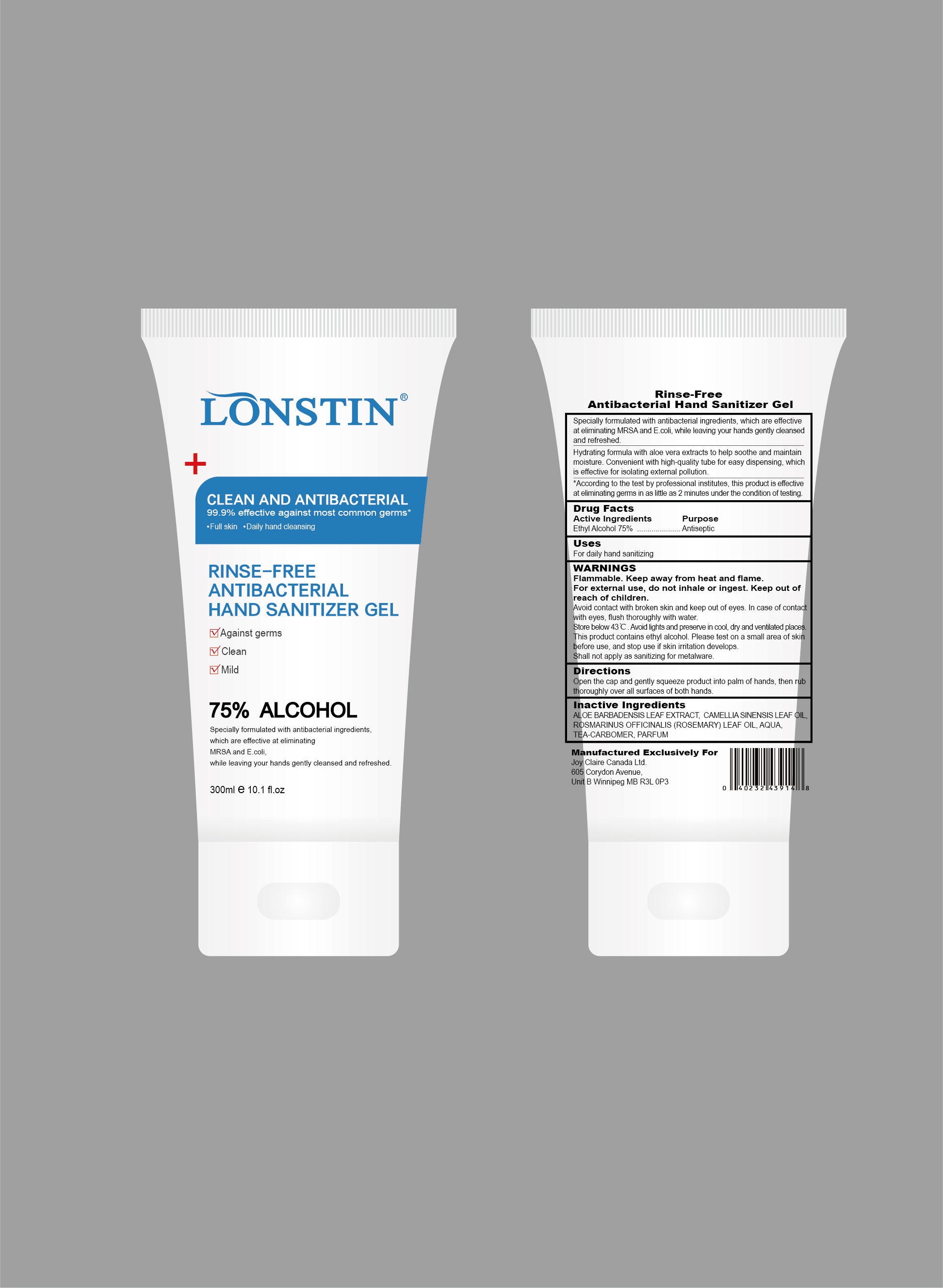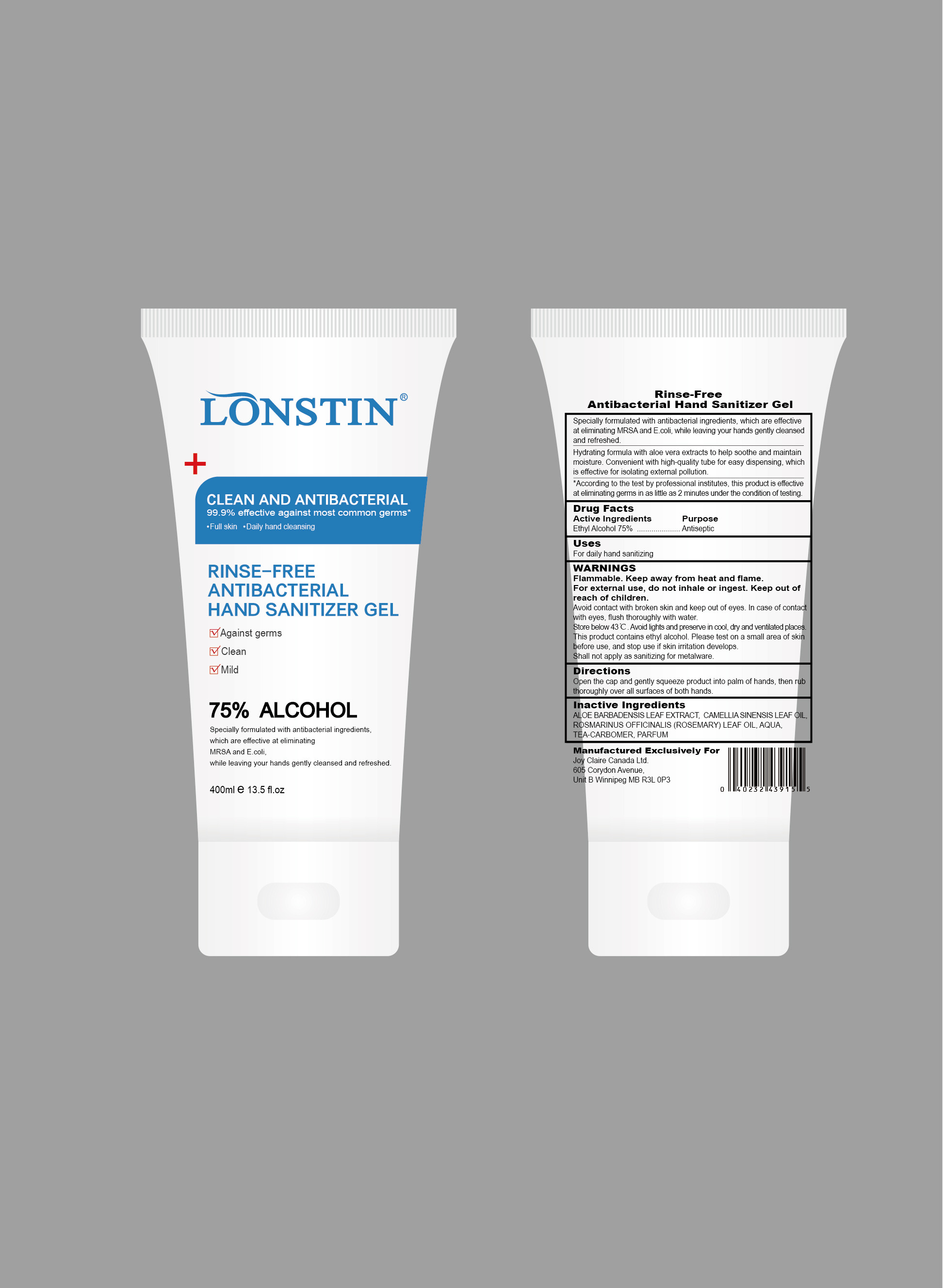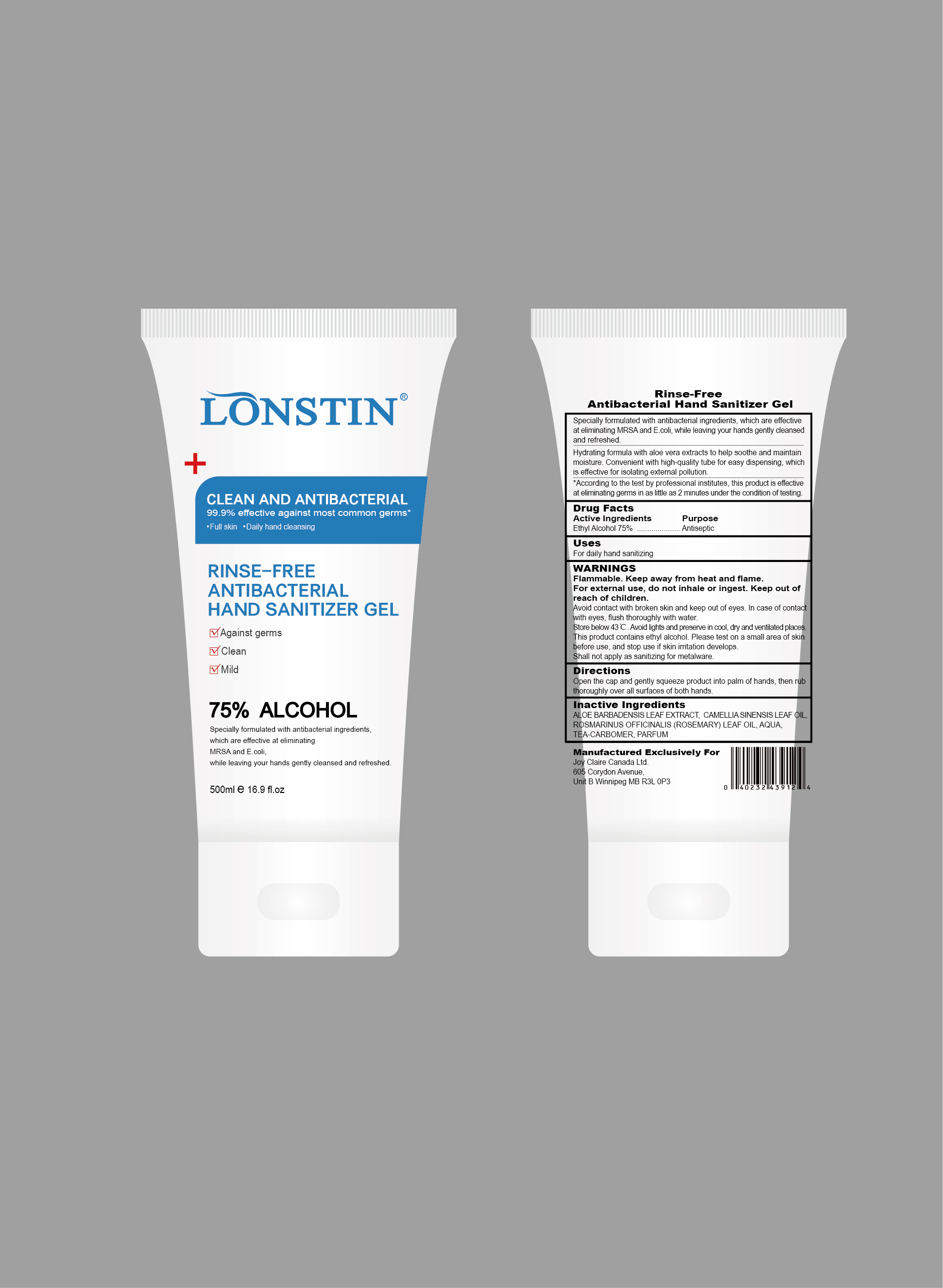 DRUG LABEL: Rinse Free Antibacterial Hand Sanitizer Gel
NDC: 74743-013 | Form: GEL
Manufacturer: Guangzhou Joy Claire Biological Technology Co., Ltd
Category: otc | Type: HUMAN OTC DRUG LABEL
Date: 20200602

ACTIVE INGREDIENTS: ALCOHOL 75 mL/100 mL
INACTIVE INGREDIENTS: ROSEMARY OIL; WATER; ALOE VERA LEAF; TEA LEAF OIL; CARBOMER HOMOPOLYMER, UNSPECIFIED TYPE

RINSE-FREE
ANTIBACTERIAL
HAND SANITIZER GEL

Active Ingredients

Ethyl Alcohol 75%

Purpose

Antiseptic

Uses

For daily hand sanitizing

WARNINGS

Flammable.Keep away from heat and flame.

For external use,do not inhale or ingest.Keep out of reach of children.

Avoid contact with broken skin and keep out of eyes.In case of contact with eyes, flush thoroughly with water.

Store below 43℃.Avoid lights and preserve in cool, dry and ventilated places.

This product contains ethyl alcohol.Please test on a small area of skin before use, and stop use if skin irritation develops.

Shall not apply as sanitizing for metalware.

Directions

Open the cap and gently squeeze product into palm of hands,then rub thoroughly over all surfaces of both hands.

Inactive Ingredients

ALOE BARBADENSIS LEAF EXTRACT, CAMELLIA SINENSIS LEAF OIL,ROSMARINUS OFFICINALIS(ROSEMARY) LEAF OIL, AQUA,TEA-CARBOMER,PARFUM